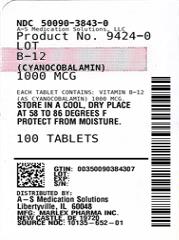 DRUG LABEL: B - 12
NDC: 50090-3843 | Form: TABLET
Manufacturer: A-S Medication Solutions
Category: other | Type: DIETARY SUPPLEMENT
Date: 20210301

ACTIVE INGREDIENTS: CYANOCOBALAMIN 1000 ug/1 1
INACTIVE INGREDIENTS: ANHYDROUS DIBASIC CALCIUM PHOSPHATE; MANNITOL; MICROCRYSTALLINE CELLULOSE; SILICON DIOXIDE; STEARIC ACID; MAGNESIUM STEARATE; HYPROMELLOSE, UNSPECIFIED

B-12 Cyanocobalamin

Supplement Facts

Serving Size: 1 Tablet

Amount Per Tablet % Daily Value

Vitamin B-12 as (Cyanocobalamin)……………………..1,000mcg……………………..41,667%

Active Ingredient (in each tablet)

Vitamin B-12 (as Cyanocobalamin)

Purpose

Dietary Supplement

Uses

Dietary Supplement

Warning:

Do not exceed recommended dosage. Consult your physician before taking this product if you have vascular disease (such as heart disease or history of stroke) or diabetes, are pregnant or nursing, taking medication, facing surgery, have bleeding problems, or undergoing any treatment which may affect the ability of blood to clot

In case of accidental overdose, call a doctor or poison control center immediately. (1-800-222-1222)

Keep out of the reach of children.

Directions

Adults and Children 18 years and over:

1,000 mcg (1 tablet) daily preferably with a meal or as directed by your doctor

Children under 18 years:

Consult your doctor

Other Information:

- Store in a cool, dry place at controlled room temperature 15-30ºC (58-86ºF)
- Protect from moisture
- Store in original container for better identification
- Use by expiration date on package

Inactive Ingredients:

Dicalcium Phosphate, Mannitol, Microcrystalline Cellulose, Silicon Dioxide, Stearic Acid, Colloidal Silicon Dioxide, Magnesium Stearate, Hypromellose

Manufactured for/Distributed by:
Marlex Pharmaceuticals, Inc.,
65 Lukens Drive
New Castle, DE 19720